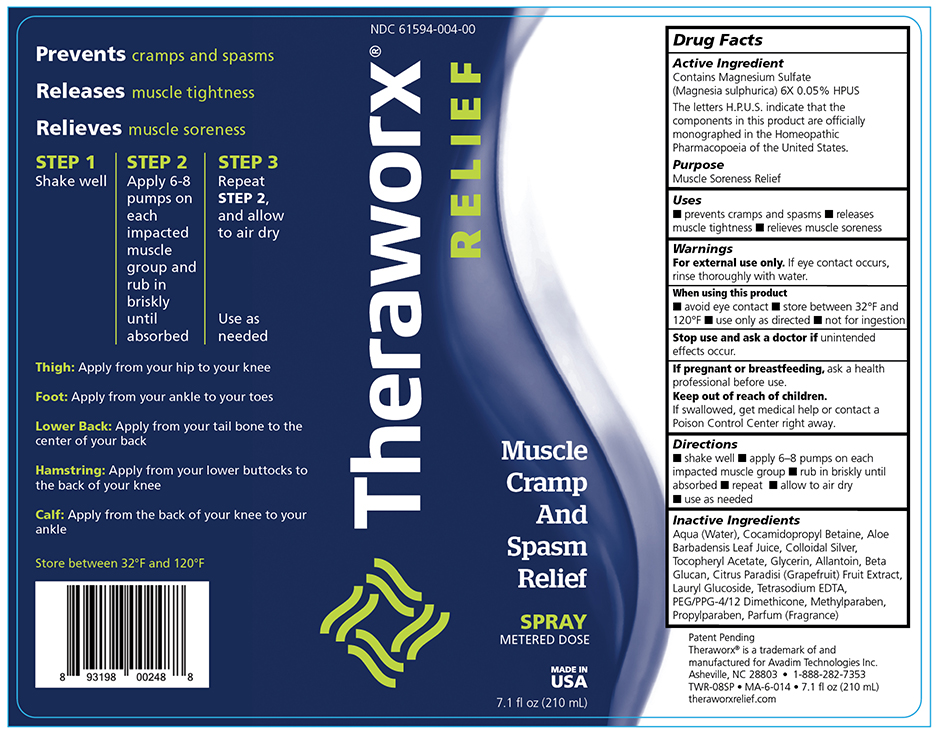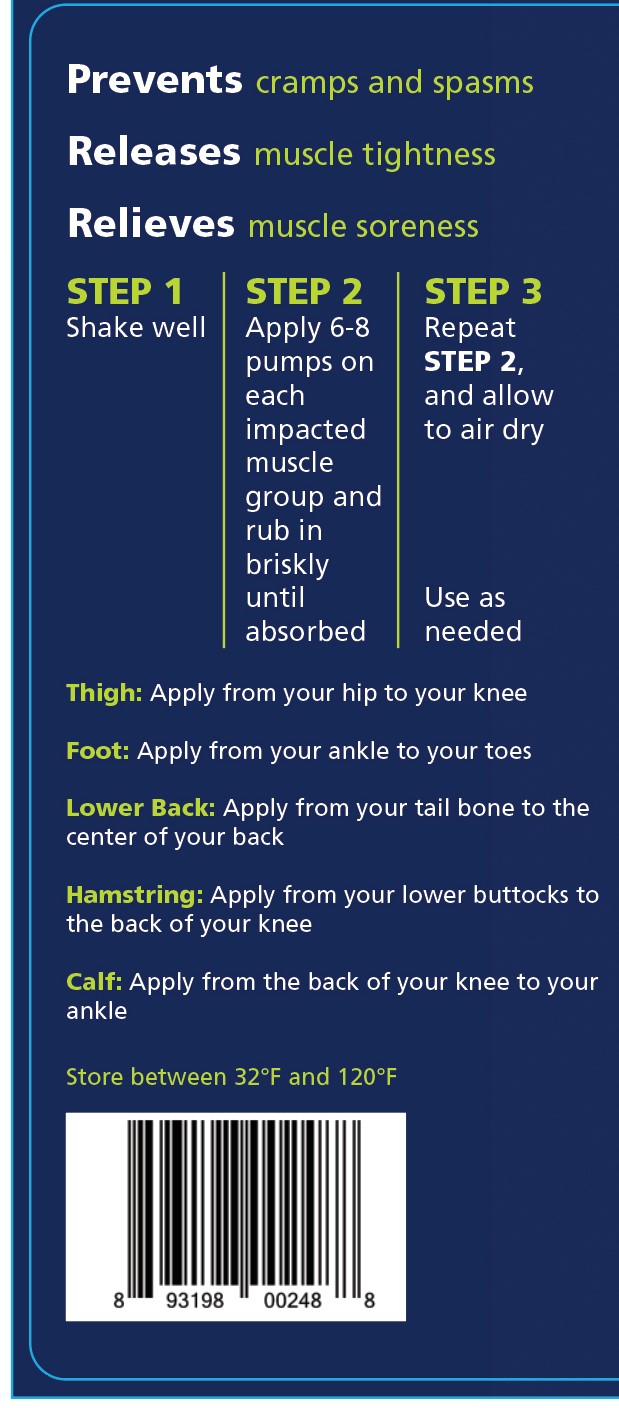 DRUG LABEL: Theraworx Relief Muscle Cramp and Spasm Relief
NDC: 71064-0004 | Form: SPRAY, METERED
Manufacturer: Relion Manufacturing
Category: homeopathic | Type: HUMAN PRESCRIPTION DRUG LABEL
Date: 20201207

ACTIVE INGREDIENTS: MAGNESIUM SULFATE HEPTAHYDRATE 6 [hp_X]/1 mL
INACTIVE INGREDIENTS: METHYLPARABEN

Theraworx Relief Muscle Cramp and Spasm Relief

0004 Bottle Label